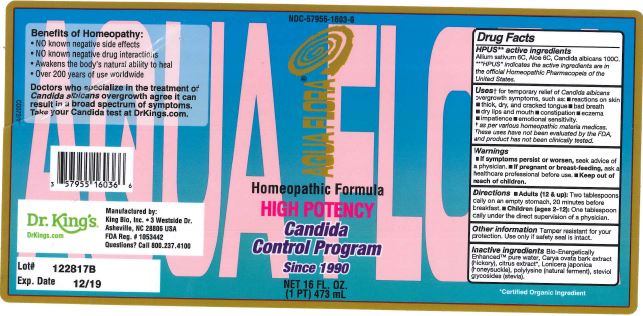 DRUG LABEL: Aqua Flora High Potency
NDC: 57955-1603 | Form: LIQUID
Manufacturer: King Bio Inc
Category: homeopathic | Type: HUMAN OTC DRUG LABEL
Date: 20180214

ACTIVE INGREDIENTS: GARLIC 6 [hp_C]/473 mL; ALOE 6 [hp_C]/473 mL; CANDIDA ALBICANS 100 [hp_C]/473 mL
INACTIVE INGREDIENTS: WATER; CARYA OVATA BARK; CITRUS BIOFLAVONOIDS; LONICERA JAPONICA FLOWER; POLYEPSILON-LYSINE (4000 MW); REBAUDIOSIDE A

Aqua Flora High potency

HPUS Active Ingredients

Allium sativum 6C, Aloe 6C, Candida albicans 100C

PURPOSE

For temporary relief of Candida albicans overgrowth symptoms, such as:

reactions on skin
thick, dry, and cracked tongue
bad breath
dry lips and mouth
constipation
eczema
impatience
emotional sensitivity

Inactive Ingredients

Bio-Energetically Enhanced pure water, Carya ovata bark extract (hickory), citrus extract, Lonicer japonica(honeysuckle), polylysine(natual ferment), steviol glycosides (stevia).

Directions

Adults(12& up): Two tablespoons daily on an empty stomach, 20 minutes before breakfast.

Children(ages 2-12): One tablespoon daily under the direct supervision of a physician.

Uses

For temporary relief of Candida albicans overgrowth symptoms, such as:

- reactions on skin
- thick, dry, and cracked tongue
- bad breath
- dry lips and mouth
- constipation
- eczema
- impatience
- emotional sensitivity

Warnings

If symptoms persist or worsen, seek advice of a physician.

If pregnant or breast-feeding, ask a healthcare professional before use.

Other Information

Tamper resistant for your protection. Use only if safety seal is intact.

Keep out of reach of children